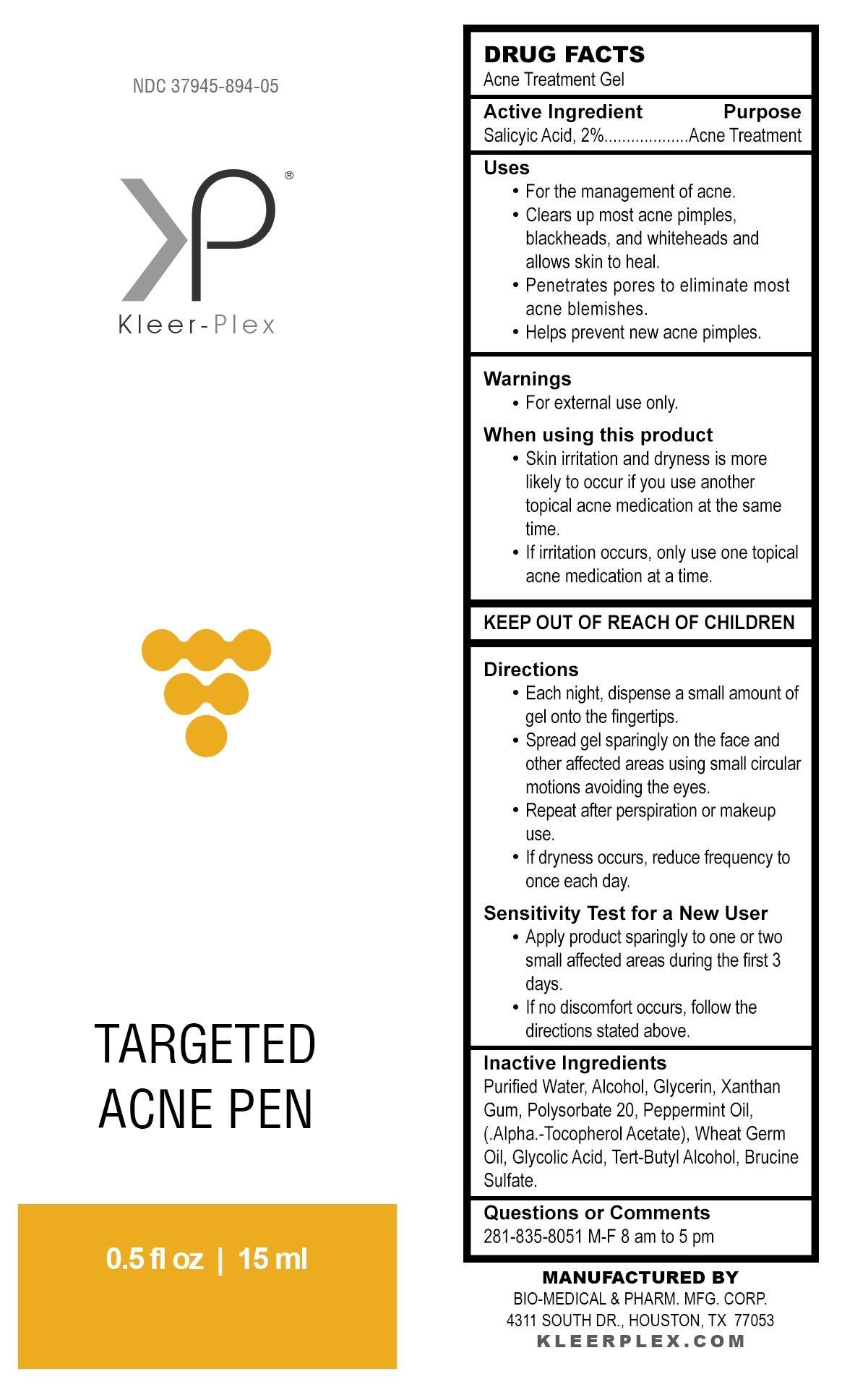 DRUG LABEL: KLEER-PLEX TARGETED ACNE PEN
NDC: 37945-894 | Form: GEL
Manufacturer: Bio-Medical & Pharmaceutical Manufacturing Corporation
Category: otc | Type: HUMAN OTC DRUG LABEL
Date: 20221213

ACTIVE INGREDIENTS: SALICYLIC ACID 20 mg/1 mL
INACTIVE INGREDIENTS: BRUCINE SULFATE; WATER; ALCOHOL; GLYCERIN; XANTHAN GUM; PEPPERMINT OIL; .ALPHA.-TOCOPHEROL ACETATE; WHEAT GERM OIL; GLYCOLIC ACID; TERT-BUTYL ALCOHOL; POLYSORBATE 20

Drug Facts

Acne Treatment Gel

Active Ingredients

Salicylic Acid, 2%

Purpose

Acne Treatment

Use

For the management of acne.
Clears up most acne pimples, blackheads, and whiteheads and allows skin to heal.
Penetrates pores to eliminate most acne blemishes.
Helps prevent new acne pimples.

Warnings

For external use only.

When using this product

Skin irritation and dryness is more likely to occur if you use another topical acne medication at the same time.
If irritation occurs, only use one topical acne medication at a time.

Keep out of reach of children

Directions

Each night, dispense a small amount of gel onto the fingertips.
Spread gel sparingly on the face and other affected areas using small circular motions avoiding the eyes.
Repeat after perspiration or makeup use.
If dryness occurs, reduce frequency to once each day.

Sensitivity test for a new user

Apply product sparingly to one or two small affected areas during the first 3 days.
If no discomfort occurs, follow the directions stated above.

Inactive Ingredients

Purified Water, Alcohol, Glycerin, Xanthan Gum, Polysorbate 20, Peppermint Oil, (.Alpha.-Tocopherol Acetate), Wheat Germ Oil, Glycolic Acid, Tert-Butyl Alcohol, Brucine Sulfate.

Questions or comments

281-835-8051

M-F 8 AM to 5 PM